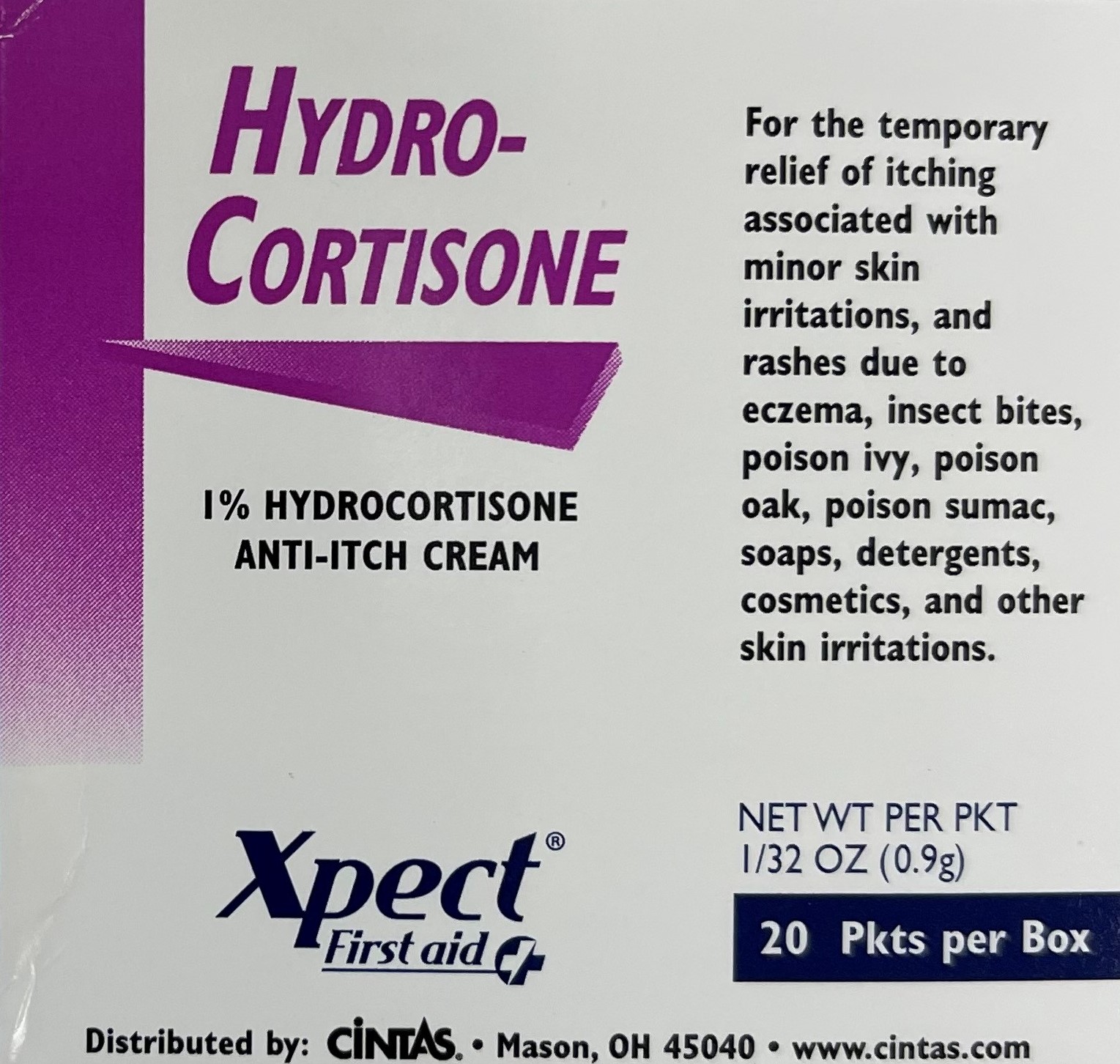 DRUG LABEL: Anti-itch cream
NDC: 82940-220 | Form: CREAM
Manufacturer: Shares inc
Category: otc | Type: HUMAN OTC DRUG LABEL
Date: 20220819

ACTIVE INGREDIENTS: HYDROCORTISONE ACETATE 0.01 g/1 g
INACTIVE INGREDIENTS: PROPYLPARABEN; EDETATE DISODIUM; WATER; TROLAMINE; METHYLPARABEN; MINERAL OIL; CETYL ALCOHOL; CITRIC ACID MONOHYDRATE; DIAZOLIDINYL UREA; GLYCERIN; GLYCERYL MONOSTEARATE; POLYETHYLENE GLYCOL, UNSPECIFIED; PROPYLENE GLYCOL; STEARIC ACID

Hydrocortisone Cream

Active ingredients (in each packet)

Hydrocortisone acetate 1%

Purpose

anti-itch cream

Uses

temporarily relieves itching associated with minor skin irritations and rashes due to:

- eczema
- insect bites
- poison ivy, oak, or sumac
- soaps, detergents, or cosmetics
- jewelry

Warnings

for external use only

Do not use

- with any other hydrocortisone product unless you have consulted a doctor
- for the treatment of diaper rash, consult a doctor

When using this product

avoid contact with eyes

Stop use and ask a doctor if

- condition worsens
- symptoms persist for more than 7 days
- symptoms clear up and occur again within a few days

Keep out of reach of children

If swallowed, get medical help or contact a Poison Control Center right away

Directions

Adults and children 2 years and over - apply to affected area not more than 3 to 4 times daily

children under 2 years - do not use

Other information

- do not use if package is torn, cut or opened
- store at room tempreature (do not freeze)
- see packet for Lot Number and expiration date

Inactive ingredients

cetyl alcohol, citric acid, diazolidinyl urea, edetate disodium, glycerin, glyceryl monostearate, methylparaben, mineral oil, polyethylene glycol, propylene glycol, propylparaben, purified water, stearic acid, trolamine

Questions

1-877-973-2811 Monday - Friday 8:00 AM to 5:00 PM

PACKAGE LABEL

Hydrocortisone

1% hydrocortisone anti-itch cream

Net wt per pkt 1/32 oz (0.9 g)

20 pkts per box